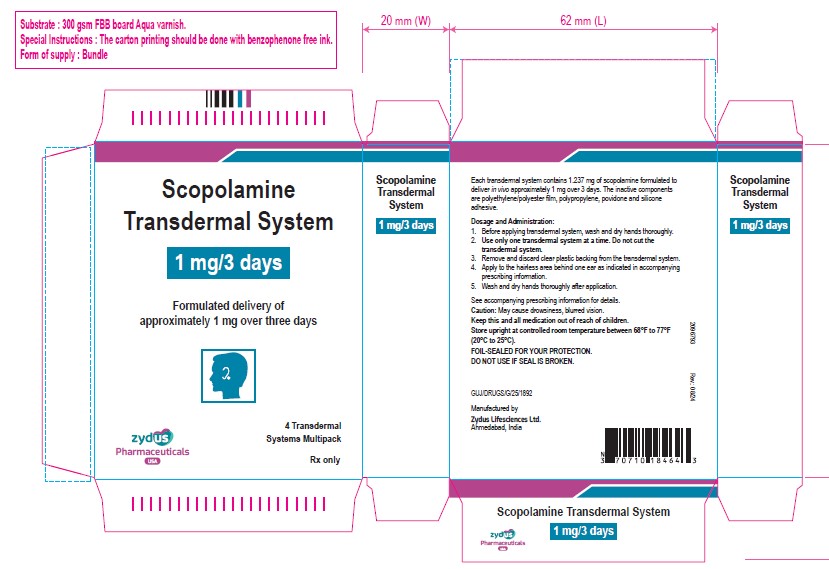 DRUG LABEL: Scopolamine
NDC: 70771-1787 | Form: PATCH, EXTENDED RELEASE
Manufacturer: Zydus Lifesciences Limited
Category: prescription | Type: HUMAN PRESCRIPTION DRUG LABEL
Date: 20250823

ACTIVE INGREDIENTS: SCOPOLAMINE 1 mg/3 d
INACTIVE INGREDIENTS: POVIDONE K30; DIMETHICONE

SCOPOLAMINE transdermal system

PACKAGE LABEL.PRINCIPAL DISPLAY PANEL

Scopolamine transdermal system, 1 mg/3 days

Carton of 4 transdermal systems

NDC 70771-1787-4

Rx only